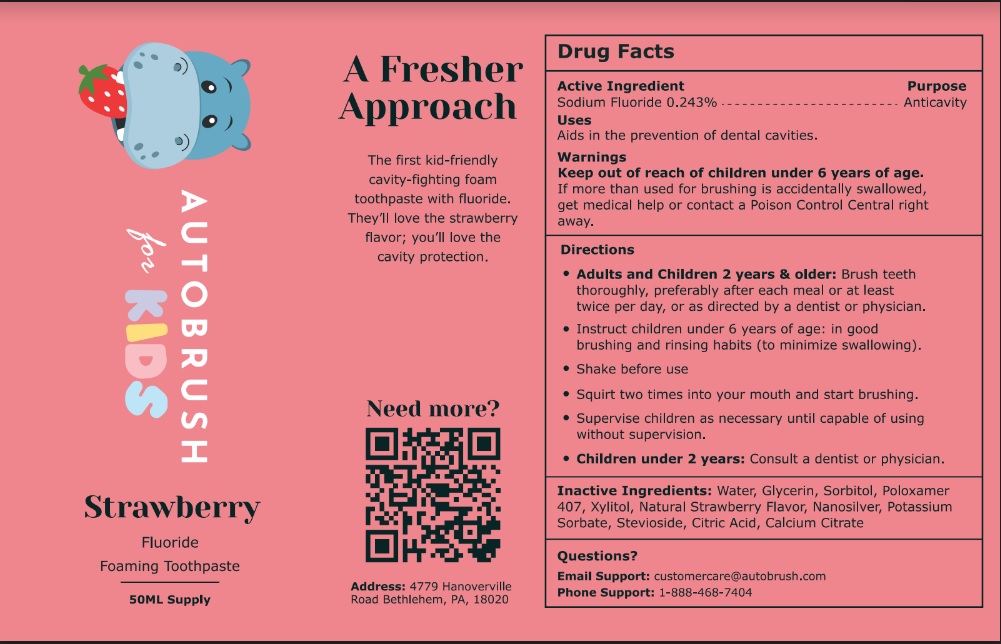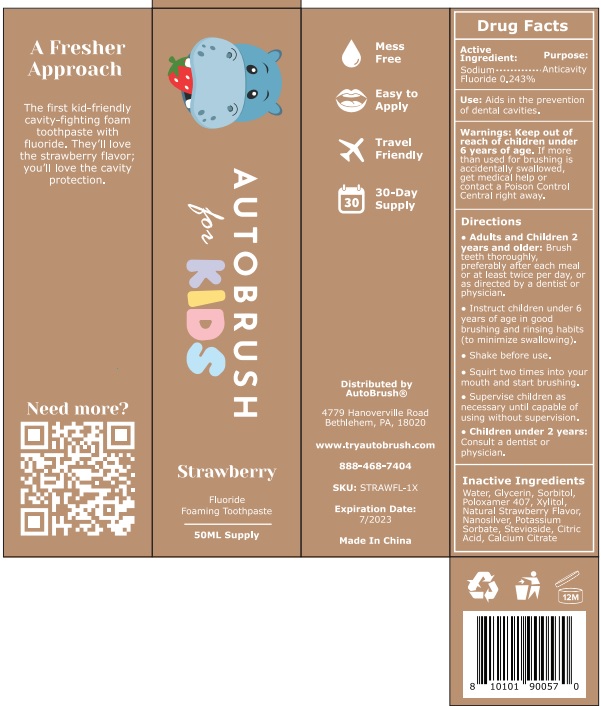 DRUG LABEL: AutoBrush strawberry
NDC: 82913-002 | Form: LIQUID
Manufacturer: Lander Enterprises, LLC
Category: otc | Type: HUMAN OTC DRUG LABEL
Date: 20251231

ACTIVE INGREDIENTS: SODIUM FLUORIDE 0.24 g/100 mL
INACTIVE INGREDIENTS: WATER; GLYCERIN; SORBITOL; POLOXAMER 407; XYLITOL; SILVER; POTASSIUM SORBATE; STEVIOSIDE; CITRIC ACID MONOHYDRATE; CALCIUM CITRATE

Active Ingredient

Sodium Fluoride 0.24%

Purpose

Anticavity

Uses

Aids in the prevention of dental cavities.

Warnings

Keep out of reach of children under 6 years of age. If more than used for brushing
is accidentally swallowed, get medical help or contact a Poison Control Central right away.

Directions

● Adults and children 2 years of age and older: Brush teeth thoroughly, preferably
after each meal or at least twice per day, or as directed by a dentist or physician.
● Instruct children under 6 years of age in good brushing and rinsing habits (to minimize swallowing).
● Shake before use.
● Squirt two times into your mouth and start brushing.
● Supervise children as necessary until capable of using without supervision.
● Children under 2 years of age: consult a dentist or physician.

Inactive Ingredients

Aqua, Glycerin, Sorbitol, Poloxamer, Xylitol, Natural Strawberry Flavor, Nano Silver, Potassium Sorbate, Stevioside, Citric Acid, Calcium Citrate

● Questions?

● Email Support: customercare@autobrush.com
● Phone Support: 1-888-468-7404